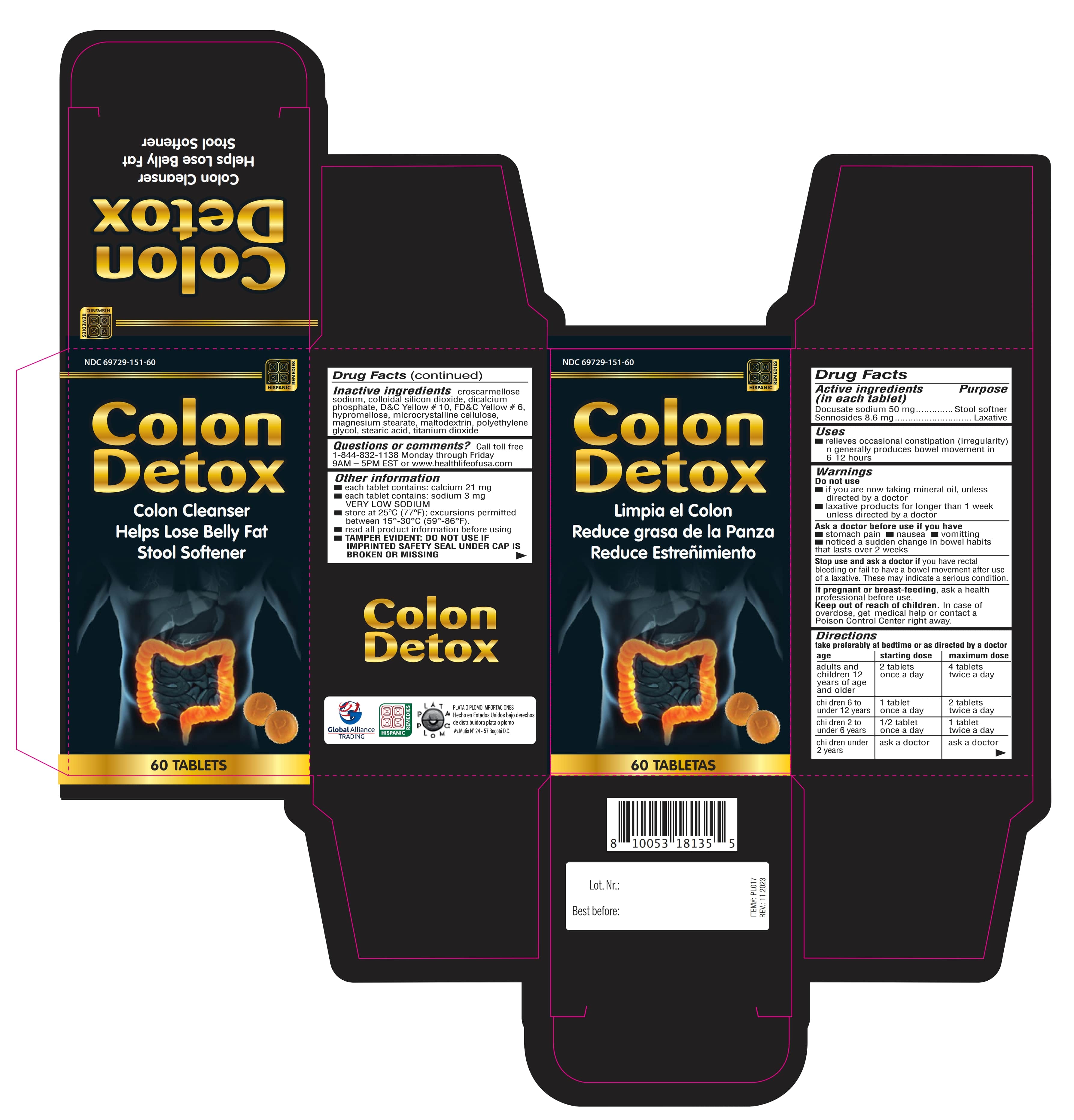 DRUG LABEL: Colon Detox
NDC: 69729-151 | Form: TABLET
Manufacturer: OPMX LLC
Category: otc | Type: HUMAN OTC DRUG LABEL
Date: 20240221

ACTIVE INGREDIENTS: DOCUSATE SODIUM 50 mg/1 1; SENNOSIDES 8.6 mg/1 1
INACTIVE INGREDIENTS: CELLULOSE, MICROCRYSTALLINE; MALTODEXTRIN; CROSCARMELLOSE SODIUM; POLYETHYLENE GLYCOL, UNSPECIFIED; STEARIC ACID; SILICON DIOXIDE; D&C YELLOW NO. 10; TITANIUM DIOXIDE; ANHYDROUS DIBASIC CALCIUM PHOSPHATE; HYPROMELLOSE, UNSPECIFIED; MAGNESIUM STEARATE; FD&C YELLOW NO. 6

Colon Detox

Active Ingredients

Purpose

Active ingredients (in each tablet) | Purpose
Docusate sodium 50 mg | Stool softner
Sennosides 8.6 mg | Laxative

Uses

For relief of occasional constipation (irregularity). This product generally produces bowel movement in 6 to 12 hours.

Warnings

Do not use

- if you are presently taking mineral oil, unless directed by a doctor.
- laxative products should not be used for a period longer than 1 week unless directed by a doctor.

Ask a doctor before use if you have

- stomach pain
- nausea
- vomitting
- noticed a sudden change in bowel habits that lasts over 2 weeks

Stop use and ask a doctor if

you have rectal bleeding or failure to have a bowel movement after use of a laxative. These may indicate a serious condition.

If pregnant or breast-feeding

ask a health professional before use.

Keep out of reach of children

In case of overdose, get medical help or contact a Poison Control Center right away.

Directions

take preferably at bedtime or as directed by a doctor

age | starting dose | maximum dose
adults and children 12 years of age and older | 2 tablets once a day | 4 tablets twice a day
children 6 to under 12 years | 1 tablet once a day | 2 tablets twice a day
children 2 to under 6 years | 1/2 tablet once a day | 1 tablet twice a day
children under 2 years | ask a doctor | ask a doctor

Other information

- each tablet contains: calcium 21 mg
- each tablet contains: sodium 3 mg VERY LOW SODIUM
- store at 25°C (77°F); excursions permitted between 15°- 30°C (59°- 86°F).
- read all product information before using
- TAMPER EVIDENT: DO NOT USE IF IMPRINTED SAFETY SEAL UNDER CAP IS BROKEN OR MISSING

Inactive ingredients

croscarmellose sodium, colloidal silicon dioxide, dicalcium phosphate, D&C Yellow #10, FD&C Yellow #6, hypromellose, microcrystalline cellulose, magnesium stearate, maltodextrin, polyethylene glycol, stearic acid, titanium dioxide.

Questions or comments?

Call toll free 1-844-832-1138 Monday through Friday 9AM-5PM EST or https://www.opmx.us

Colon Detox

Colon Cleanser

Helps Lose Belly Fat

Stool Softener

60 Tablets